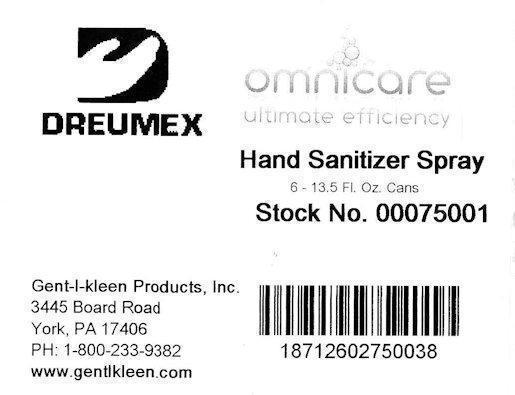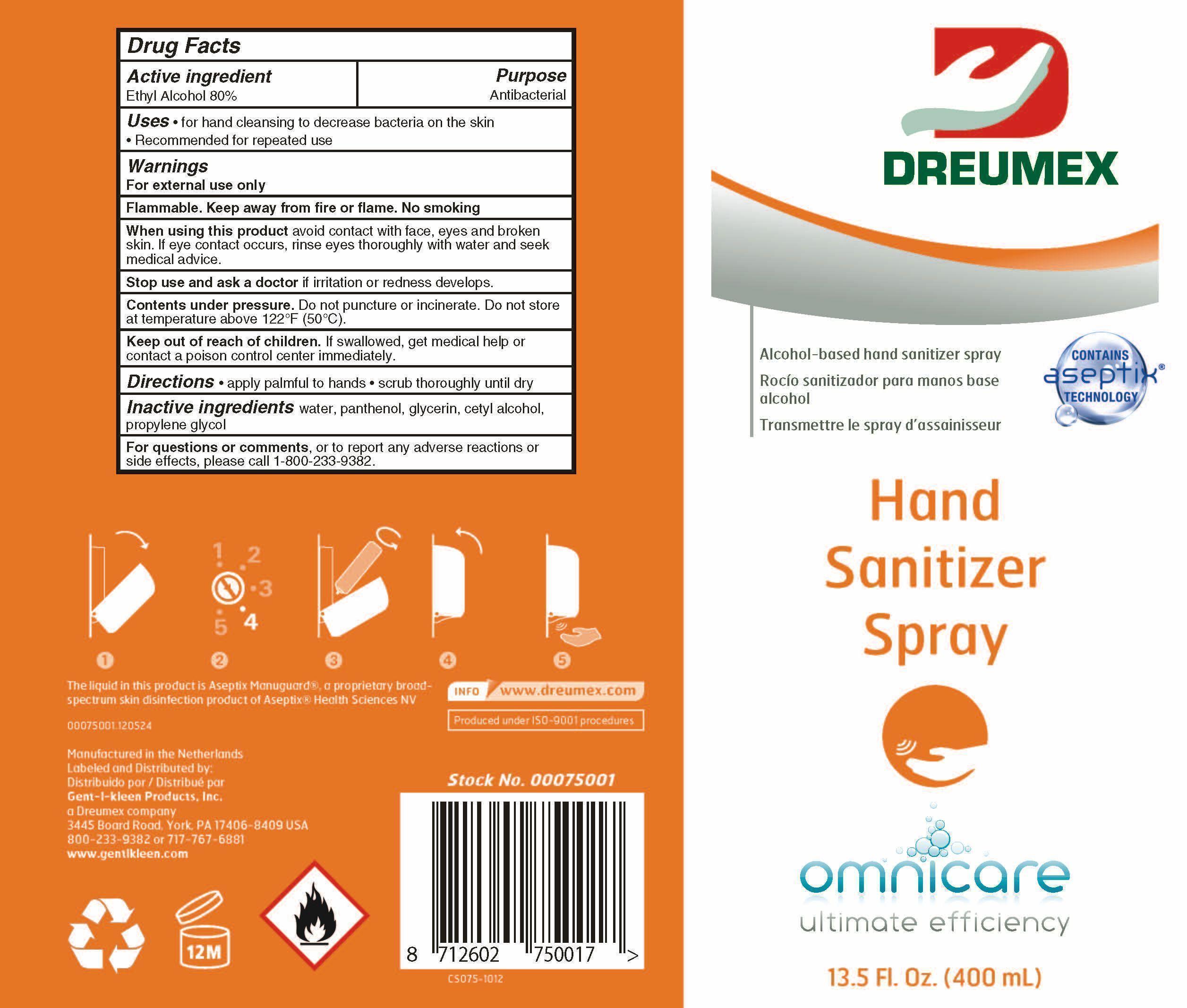 DRUG LABEL: Dreumex Omnicare Hand Sanitizer
NDC: 53305-065 | Form: SPRAY
Manufacturer: Dreumex USA, Inc.
Category: otc | Type: HUMAN OTC DRUG LABEL
Date: 20180905

ACTIVE INGREDIENTS: ALCOHOL 800 mg/1.2 mL
INACTIVE INGREDIENTS: WATER 400 mg/1.2 mL

Active Ingredient

Ethyl Alcohol, 80%

Purpose

Antibacterial

Uses

For hand cleaning to decrease bacteria on the skin.

Recommended for repeated use.

Warnings

For external use only.

Flammable. Keep away from fire or flame. No Smoking.

When using this product

avoid contact with face, eyes and broken skin. If eye contact occurs, rinse eyes thoroughly with water and seek medical advice.

Stop use and ask a doctor

if irritation or redness develops.

Contents under pressure.

Do not puncture or incinerate. Do not store at temperatures above 120°F (50°C).

Keep out of reach of children.

If swallowed get medical help, or contact a poison control center immediately.

Directions

- apply a palmful to hands
- scrub thoroughly until dry

Inactive Ingredients

water panthenol, glycerin, cetyl alcohol, propylene glycol.

For questions or comments

or to report any adverse reactions or side effects, please call 1-800-233-9382.